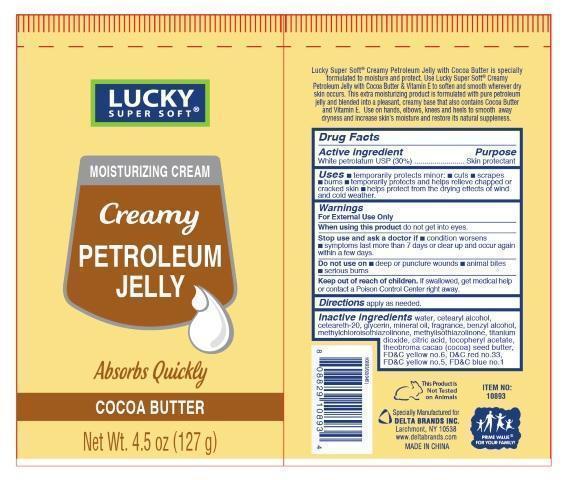 DRUG LABEL: LUCKY SUPER SOFT
NDC: 47046-170 | Form: CREAM
Manufacturer: Anicare Pharmaceuticals Pvt. Ltd.
Category: otc | Type: HUMAN OTC DRUG LABEL
Date: 20201220

ACTIVE INGREDIENTS: PETROLATUM 30 g/100 g
INACTIVE INGREDIENTS: WATER; CETOSTEARYL ALCOHOL; POLYOXYL 20 CETOSTEARYL ETHER; GLYCERIN; MINERAL OIL; BENZYL ALCOHOL; METHYLCHLOROISOTHIAZOLINONE; METHYLISOTHIAZOLINONE; TITANIUM DIOXIDE; CITRIC ACID MONOHYDRATE; .ALPHA.-TOCOPHEROL ACETATE; COCOA BUTTER; FD&C YELLOW NO. 6; D&C RED NO. 33; FD&C YELLOW NO. 5; FD&C BLUE NO. 1

super soft cream

Active ingredient

White petrolatum USP (30%)

Purpose

Skin protectant

Uses

■ temporarily protects minor ■ cuts ■ scrapes ■ burns ■ temporarily protects and helps relieve chapped or cracked skin ■ helps prevent and protect from the drying effects of wind and cold weather

Warnings

For External Use Only

When using this product

do not get into eyes

Stop use and ask a doctor if

■ condition worsens ■ symptoms last more than 7 days or clear up and occur again in a few days

Do not use on

■ deep or puncture wounds ■ animal bites ■ serious burns

Keep out of reach of children

If swallowed, get medical help or contact a Poison Control Center right away

Directions

apply as needed

Inactive ingredients

water, cetearyl alcohol, ceteareth 20, glycerin, mineral oil, fragrance, benzyl alcohol, methylchloroisothaizolinone, methylisothaizolinone, titanium dioxide, citric acid, tocopheryl acetate, theobroma cacao seed butter, FDC yellow no 6, DC red no 33, FDC yellow no 5, FDC blue no 1